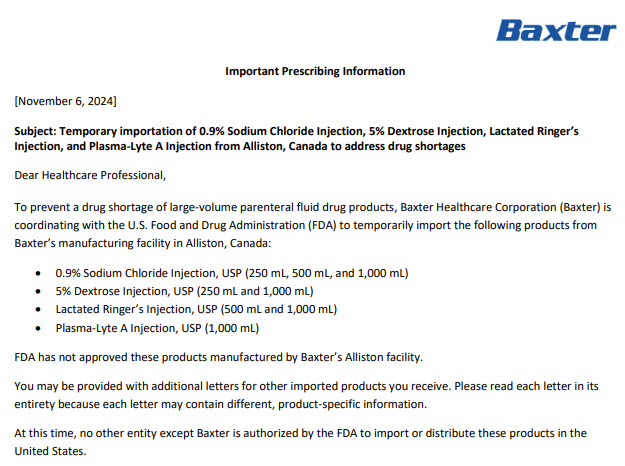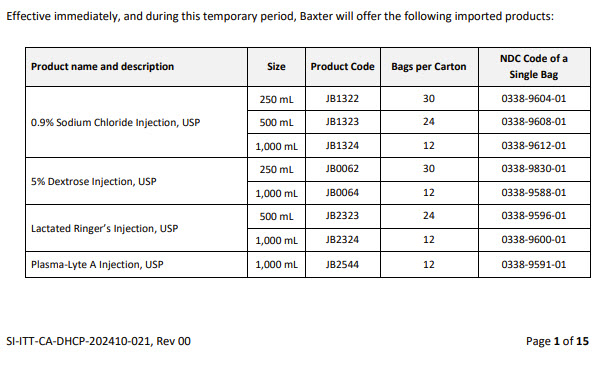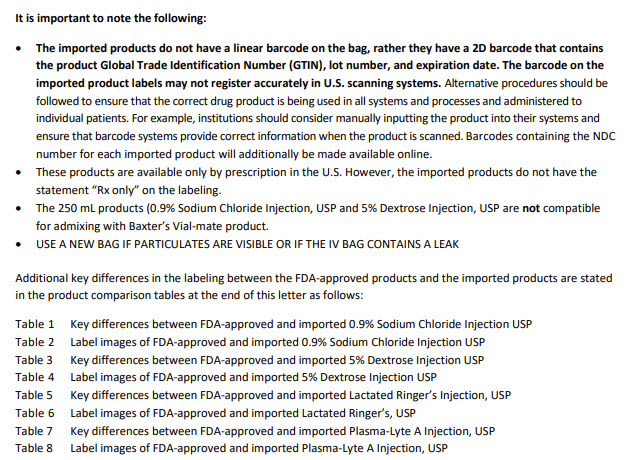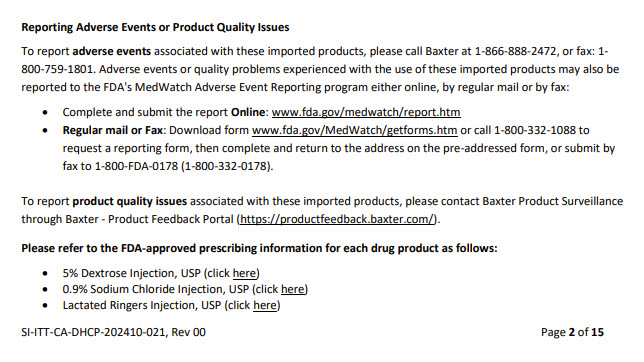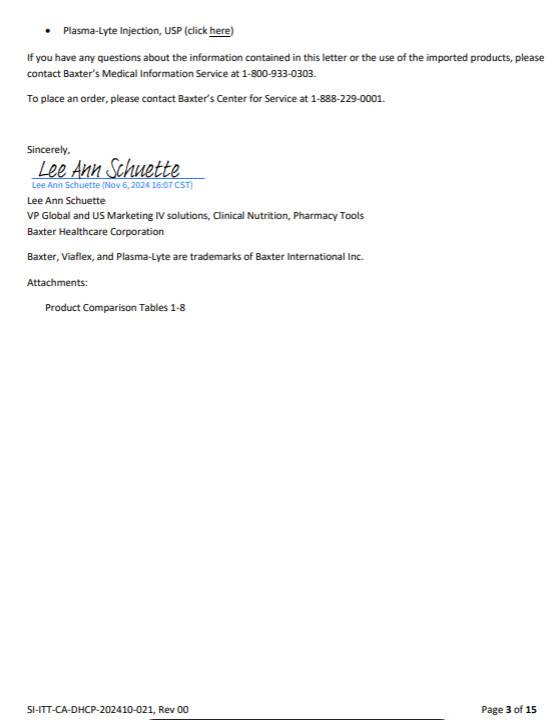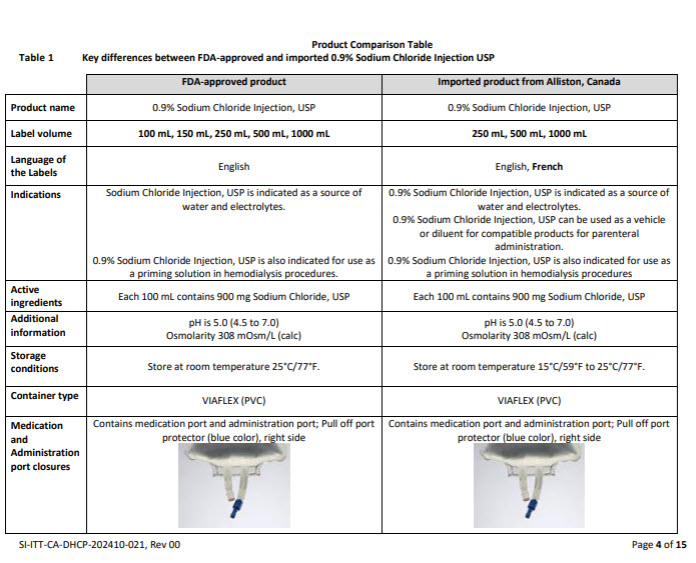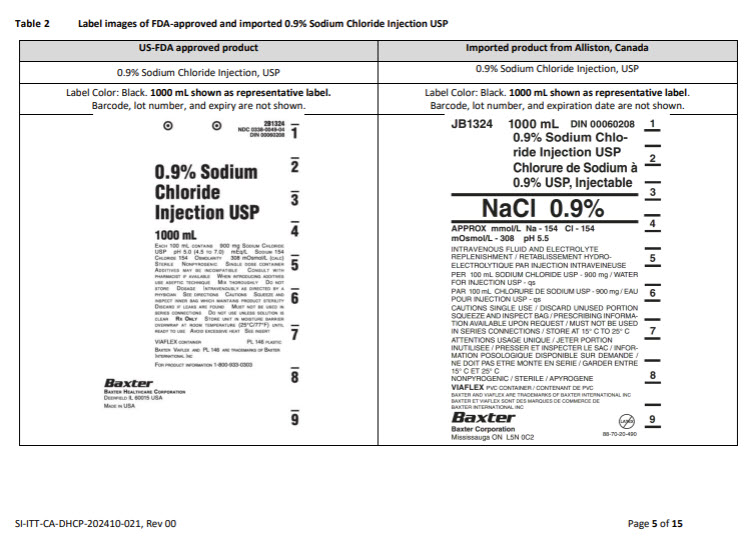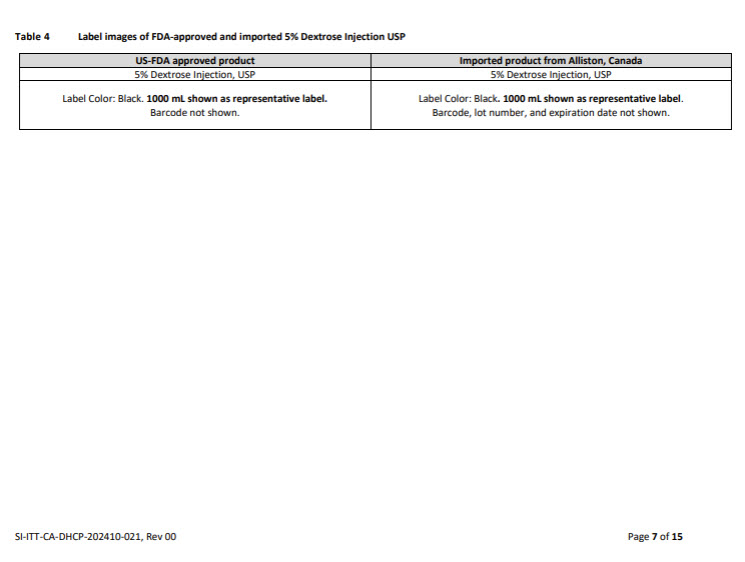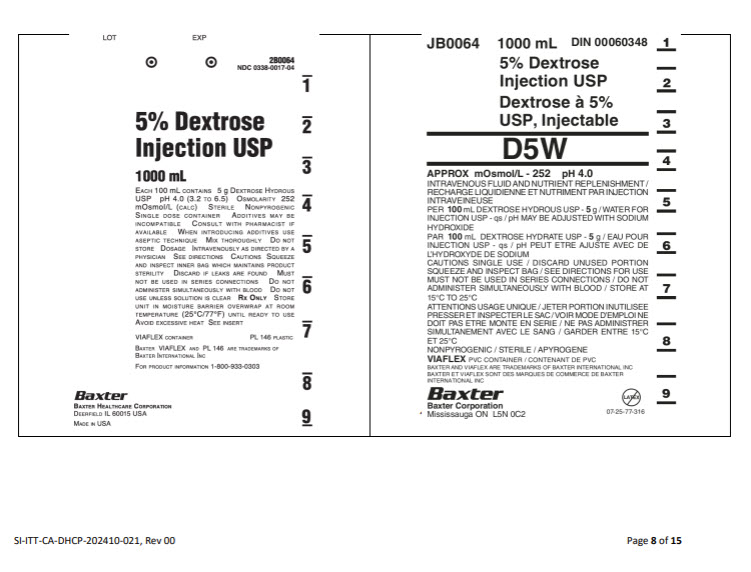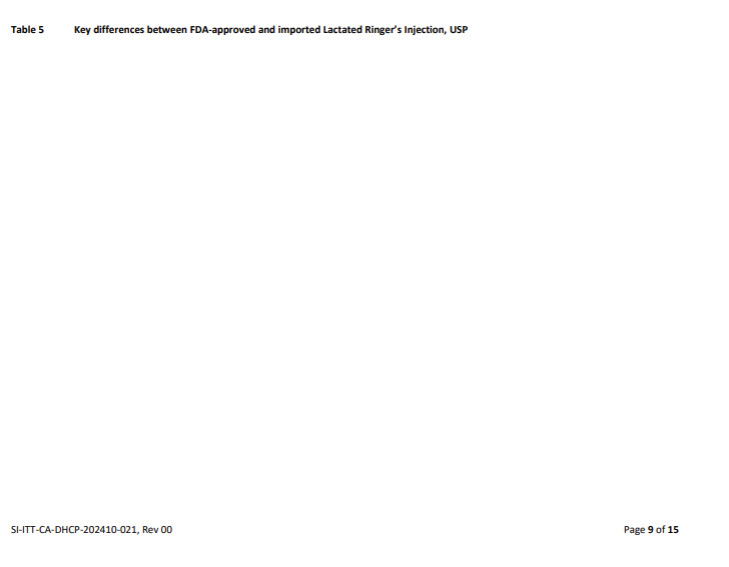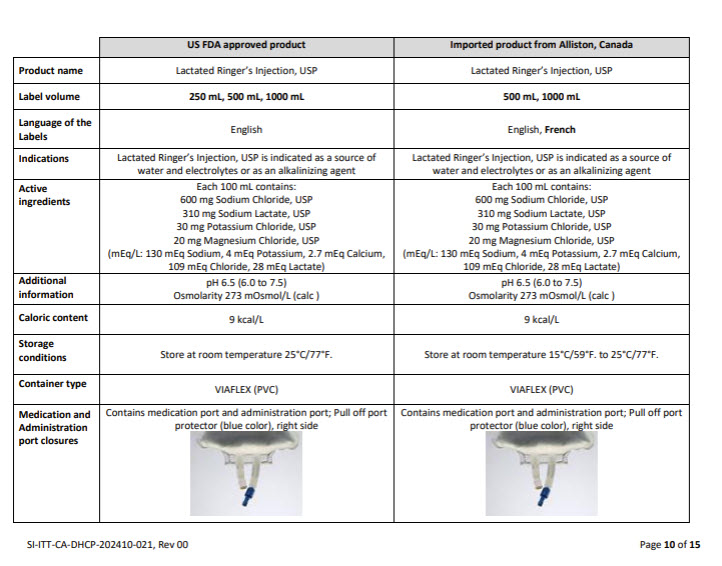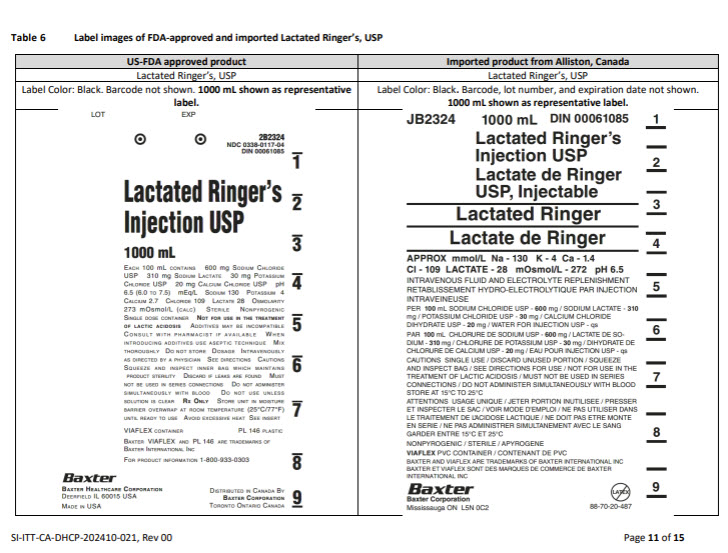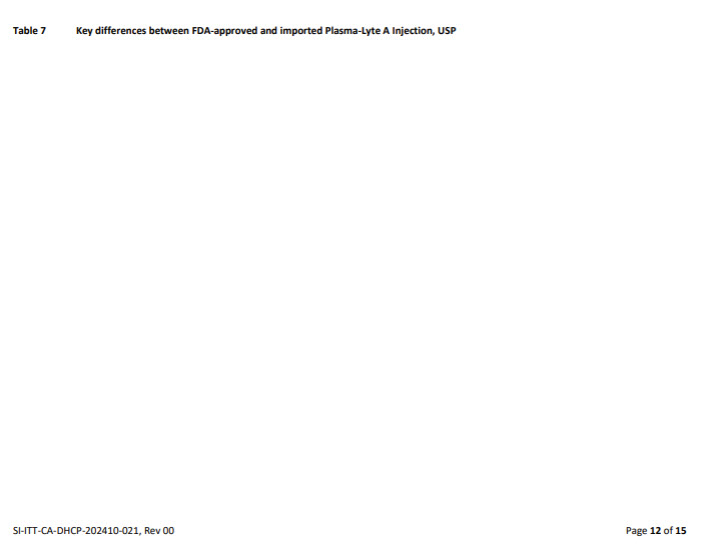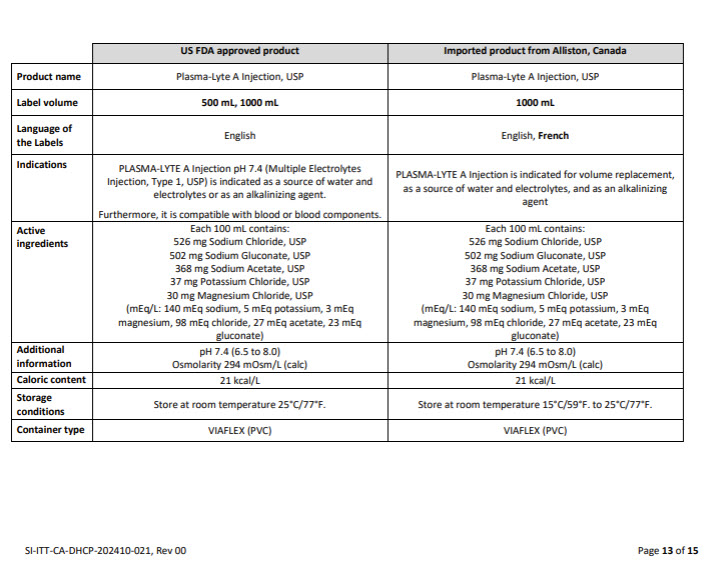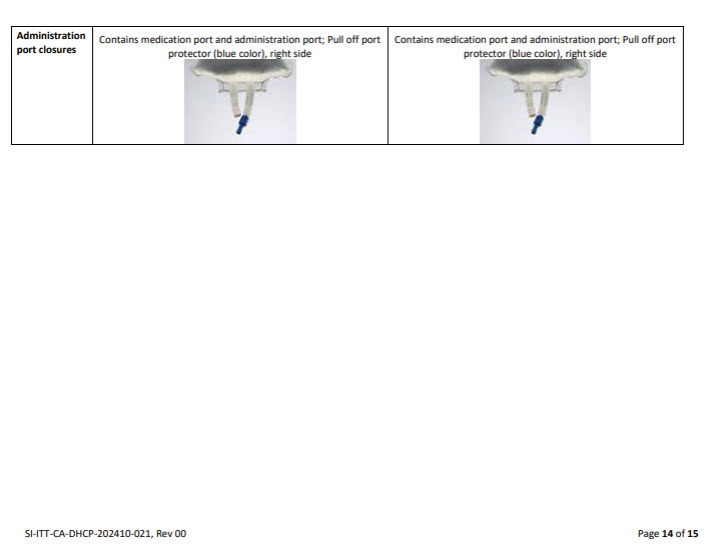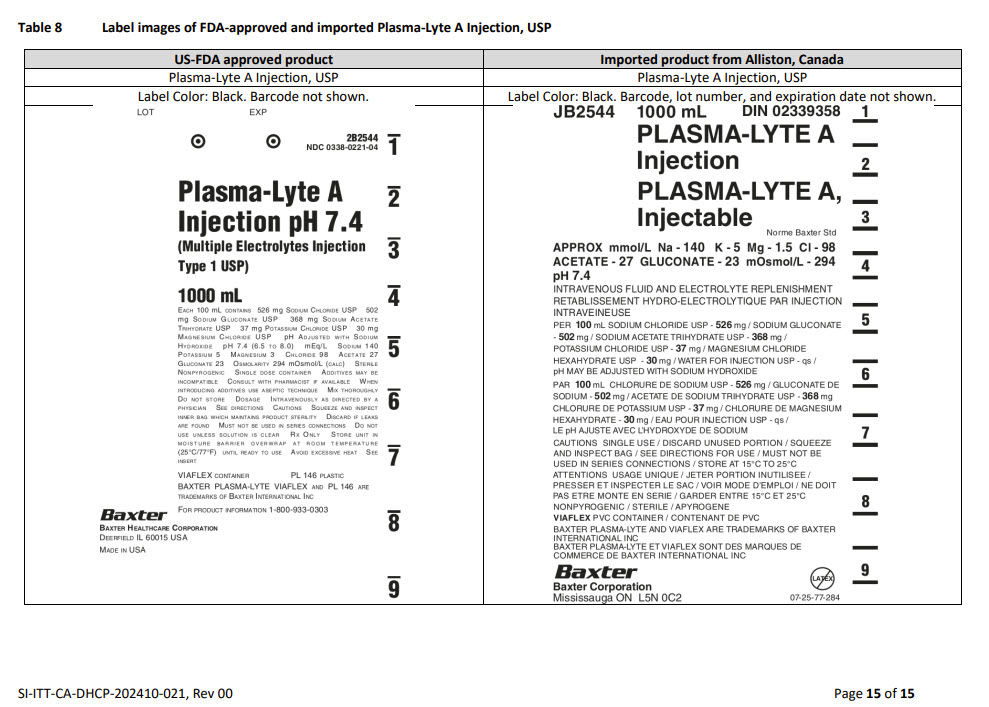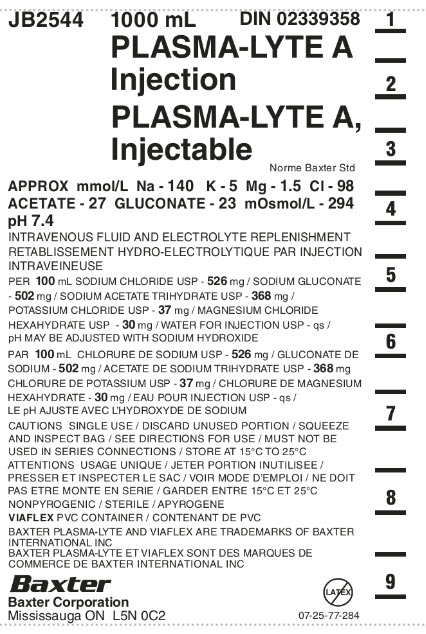 DRUG LABEL: Plasma-Lyte A
NDC: 0338-9591 | Form: INJECTION, SOLUTION
Manufacturer: Baxter Healthcare Company
Category: prescription | Type: HUMAN PRESCRIPTION DRUG LABEL
Date: 20241014

ACTIVE INGREDIENTS: SODIUM CHLORIDE 526 mg/100 mL; SODIUM GLUCONATE 502 ug/100 mL; SODIUM ACETATE 368 mg/100 mL; POTASSIUM CHLORIDE 37 mg/100 mL; MAGNESIUM CHLORIDE 30 mg/100 mL
INACTIVE INGREDIENTS: WATER; SODIUM HYDROXIDE

plasma-lyte a Injection

PACKAGE/LABEL PRINCIPAL DISPLAY PANEL

Container Label

JB2544 1000 mL DIN 02339358

PLASMA-LYTE A
INJECTION

PLASMA-LYTE A,
Injectable

Norme Baxter Std

APPROX mmol/L Na – 140 K – 5 Mg – 1.5 Cl – 98
ACETATE – 27 GLUCONATE – 23 mOsmol/L – 294
pH 7.4

INTRAVENOUS FLUID AND ELECTROLYTE REPLENISHMENT
RETABLISSEMENT HYDRO-ELECTROLYTIQUE PAR INJECTION
INTRAVEINEUSE

PER 100 mL SODIUM CHLORIDE USP – 526 mg / SODIUM GLUCONATE
- 502 mg / SODIUM ACETATE TRIHYDRATE USP – 368 mg /
POTASSIUM CHLORIDE USP – 37 mg / MAGNESIUM CHLORIDE
HEXAHYDRATE USP – 30 mg / WATER FOR INJECTION USP – qs
pH MAY BE ADJUSTED WITH SODIUM HYDROXIDE

PAR 100 mL CHLORURE DE SODIUM USP – 526 mg / GLUCONATE DE
SODIUM - 502 mg / ACETATE DE SODIUM TRIHYDRATE USP – 368 mg
CHLORURE DE POTASSIUM USP – 37 mg / CHLORURE DE MAGNESIUM
HEXAHYDRATE USP – 30 mg / EAU POUR INJECTION USP – qs
LE pH AJUSTE AVEC L’HYDROXYDE DE SODIUM

CAUTIONS SINGLE USE / DISCARD UNUSED PORTION / SQUEEZE
AND INSPECT BAG / SEE DIRECTIONS FOR USE / MUST NOT BE
USED IN SERIES CONNECTIONS / STORE AT 15°C TO 25°C

ATTENTIONS USAGE UNIQUE / JETER PORTION INUTILISEE/
PRESSER ET INSPECTER LE SAC / VOIR MODE D’EMPLOI / NE DOIT
PAS ETRE MONTE EN SERIE / GARDER ENTRE ET 15°C ET 25°C

NONPYROGENIC / STERILE / APYROGENE

VIAFLEX PVC CONTAINER / CONTENANT DE PVC

BAXTER PLASMA-LYTE AND VIAFLEX ARE TRADEMARKS OF BAXTER
INTERNATIONAL INC
BAXTER PLASMA-LYTE ET VIAFLEX SONT DES MARQUES DE
COMMERCE DE BAXTER INTERNATIONAL INC

Baxter Logo
Baxter Corporation
Mississauga ON L5C 0C2

No LATEX Label

07-25-77-284

1

_

2

_

3

_

4

_

5

_

6

_

7

_

8

_

9